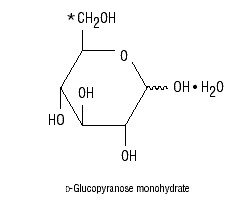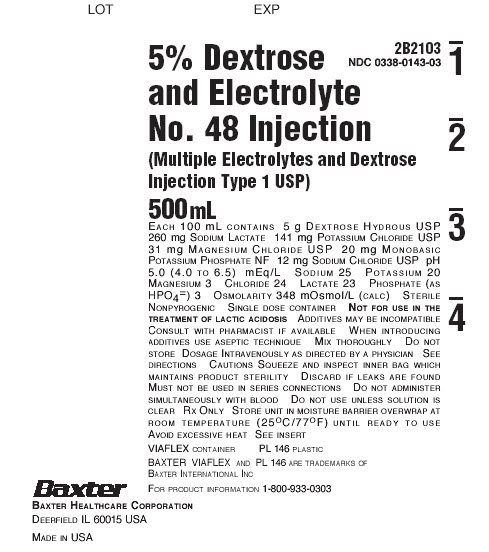 DRUG LABEL: Dextrose and Electrolyte No. 48
NDC: 0338-0143 | Form: INJECTION
Manufacturer: Baxter Healthcare Company
Category: prescription | Type: HUMAN PRESCRIPTION DRUG LABEL
Date: 20200213

ACTIVE INGREDIENTS: DEXTROSE MONOHYDRATE 5 g/100 mL; SODIUM LACTATE 260 mg/100 mL; POTASSIUM CHLORIDE 141 mg/100 mL; MAGNESIUM CHLORIDE 31 mg/100 mL; POTASSIUM PHOSPHATE, MONOBASIC 20 mg/100 mL; SODIUM CHLORIDE 12 mg/100 mL
INACTIVE INGREDIENTS: WATER

5% Dextrose and Electrolyte No. 48 Injection
(Multiple Electrolytes and Dextrose Injection, Type 1, USP)

in VIAFLEX Plastic Container

DESCRIPTION

5% Dextrose and Electrolyte No. 48 Injection (Multiple Electrolytes and Dextrose Injection, Type 1, USP) is a sterile, nonpyrogenic solution for fluid and electrolyte replenishment and caloric supply in a single dose container for intravenous administration. Each 100 mL contains 5 g Dextrose Hydrous, USP*, 260 mg Sodium Lactate (C3H5NaO3), 141 mg Potassium Chloride, USP (KCl), 31 mg Magnesium Chloride, USP (MgCl2•6H20), 20 mg Monobasic Potassium Phosphate, NF (KH2PO4), and 12 mg Sodium Chloride, USP (NaCl). It contains no antimicrobial agents. The pH is 5.0 (4.0 to 6.5).

5% Dextrose and Electrolyte No. 48 Injection (Multiple Electrolytes and Dextrose Injection, Type 1, USP) administered intravenously has value as a source of water, electrolytes, and calories. One liter has an ionic concentration of 25 mEq sodium, 20 mEq potassium, 3 mEq magnesium, 24 mEq chloride, 23 mEq lactate and 3 mEq phosphate (as HPO4^2-). The osmolarity is 348 mOsmol/L (calc). Normal physiologic osmolarity range is approximately 280 to 310 mOsmol/L. Administration of substantially hypertonic solutions (≥ 600 mOsmol/L) may cause vein damage. The caloric content is 180 kcal/L.

Dextrose is derived from corn.

The VIAFLEX plastic container is fabricated from a specially formulated polyvinyl chloride (PL 146 Plastic). The amount of water that can permeate from inside the container into the overwrap is insufficient to affect the solution significantly. Solutions in contact with the plastic container can leach out certain of its chemical components in very small amounts within the expiration period, e.g., di-2-ethylhexyl phthalate (DEHP), up to 5 parts per million. However, the safety of the plastic has been confirmed in tests in animals according to USP biological tests for plastic containers as well as by tissue culture toxicity studies.

CLINICAL PHARMACOLOGY

5% Dextrose and Electrolyte No. 48 Injection (Multiple Electrolytes and Dextrose Injection, Type 1, USP) has value as a source of water, electrolytes and calories. They are capable of inducing diuresis depending on the clinical condition of the patient.

5% Dextrose and Electrolyte No. 48 Injection (Multiple Electrolytes and Dextrose Injection, Type 1, USP) produce a metabolic alkalinizing effect. Lactate ions are metabolized ultimately to carbon dioxide and water, which requires the consumption of hydrogen cations.

INDICATIONS AND USAGE

5% Dextrose and Electrolyte No. 48 Injection (Multiple Electrolytes and Dextrose Injection, Type 1, USP) is indicated as a source of water, electrolytes, and calories or as an alkalinizing agent.

CONTRAINDICATIONS

5% Dextrose and Electrolyte No. 48 Injection (Multiple Electrolytes and Dextrose Injection, Type 1, USP) is contraindicated in patients

- with a known hypersensitivity to the product (see WARNINGS)
- with clinically significant hyperglycemia (see WARNINGS)

WARNINGS

Hypersensitivity Reactions

Hypersensitivity and infusion reactions have been reported with 5% Dextrose and Electrolyte No. 48 Injection (Multiple Electrolytes and Dextrose Injection, Type 1, USP). See ADVERSE REACTIONS.

Stop the infusion immediately if signs or symptoms of a hypersensitivity reaction develop, such as tachycardia, chest pain, dyspnea and flushing. Institute appropriate therapeutic countermeasures as clinically indicated.

Electrolyte Imbalances

Fluid Overload

Depending on the volume and rate of infusion, the intravenous administration of 5% Dextrose and Electrolyte No. 48 Injection (Multiple Electrolytes and Dextrose Injection, Type 1, USP) can cause electrolyte disturbances such as overhydration and congested states, including pulmonary congestion and edema.

Avoid 5% Dextrose and Electrolyte No. 48 Injection (Multiple Electrolytes and Dextrose Injection, Type 1, USP) in patients with or at risk for fluid and/or solute overloading. If use cannot be avoided, monitor fluid balance, electrolyte concentrations, and acid base balance, as needed and especially during prolonged use.

Hyponatremia

5% Dextrose and Electrolyte No. 48 Injection (Multiple Electrolytes and Dextrose Injection, Type 1, USP) may cause hyponatremia. 5% Dextrose and Electrolyte No. 48 Injection (Multiple Electrolytes and Dextrose Injection, Type 1, USP) is a hypertonic solution. In the body, however, glucose containing fluids can become extremely physiologically hypotonic due to rapid glucose metabolization. Monitoring of serum sodium is particularly important for hypotonic fluids.

Hyponatremia can lead to acute hyponatremic encephalopathy characterized by headache, nausea, seizures, lethargy, and vomiting. Patients with brain edema are at particular risk of severe, irreversible and life-threatening brain injury.

The risk of hospital-acquired hyponatremia is increased in patients with cardiac or pulmonary failure, and in patients with non-osmotic vasopressin release (including SIADH) treated with high volume of physiologically hypotonic 5% Dextrose and Electrolyte No. 48 Injection (Multiple Electrolytes and Dextrose Injection, Type 1, USP).

Avoid 5% Dextrose and Electrolyte No. 48 Injection (Multiple Electrolytes and Dextrose Injection, Type 1, USP) in hypervolemic or overhydrated patients. If use cannot be avoided, monitor serum sodium concentrations.

Hyperglycemia and Hyperosmolar Hyperglycemic State

Administration of solutions containing dextrose and lactate in patients with impaired glucose tolerance or diabetes mellitus may worsen hyperglycemia (see PRECAUTIONS, Pediatric Use). Administration of dextrose at a rate exceeding the patient’s utilization rate may lead to hyperglycemia, coma, and death.

Hyperglycemia is associated with an increase in serum osmolality, resulting in osmotic diuresis, dehydration and electrolyte losses.

Patients with underlying central nervous system disease and renal impairment who receive dextrose infusions, may be at greater risk of developing hyperosmolar hyperglycemic state.

Monitor blood glucose concentrations and treat hyperglycemia to maintain concentrations within normal limits while administering 5% Dextrose and Electrolyte No. 48 Injection (Multiple Electrolytes and Dextrose Injection, Type 1, USP). Insulin may be administered or adjusted to maintain optimal blood glucose concentrations.

Hypernatremia

Hypernatremia may occur with 5% Dextrose and Electrolyte No. 48 Injection (Multiple Electrolytes and Dextrose Injection, Type 1, USP). Conditions that may increase the risk of hypernatremia, fluid overload and edema (central and peripheral), include patients with: primary hyperaldosteronism; secondary hyperaldosteronism associated with, for example, hypertension, congestive heart failure, liver disease (including cirrhosis), renal disease (including renal artery stenosis, nephrosclerosis); and pre-eclampsia.

Certain medications, such as corticosteroids or corticotropin, may also increase risk of sodium and fluid retention, see PRECAUTIONS.

Avoid 5% Dextrose and Electrolyte No. 48 Injection (Multiple Electrolytes and Dextrose Injection, Type 1, USP) in patients with, or at risk for, hypernatremia. If use cannot be avoided, monitor serum sodium concentrations.

Hypermagnesemia

Avoid solutions containing magnesium, including 5% Dextrose and Electrolyte No. 48 Injection (Multiple Electrolytes and Dextrose Injection, Type 1, USP) in patients with or predisposed to hypermagnesemia, including patients with severe renal impairment and those patients receiving magnesium therapy (e.g., treatment of eclampsia and myasthenia gravis).

5% Dextrose and Electrolyte No. 48 Injection (Multiple Electrolytes and Dextrose Injection, Type 1, USP) is not indicated for the treatment of hypomagnesemia.

Acidosis

5% Dextrose and Electrolyte No. 48 Injection (Multiple Electrolytes and Dextrose Injection, Type 1, USP) is not for use for the treatment of lactic acidosis or severe metabolic acidosis in patients with severe liver and/or renal impairment.

Alkalosis

Excess administration of 5% Dextrose and Electrolyte No. 48 Injection (Multiple Electrolytes and Dextrose Injection, Type 1, USP) can result in metabolic alkalosis. Avoid 5% Dextrose and Electrolyte No. 48 Injection (Multiple Electrolytes Injection, Type 1, USP) in patients with alkalosis or at risk for alkalosis.

5% Dextrose and Electrolyte No. 48 Injection (Multiple Electrolytes and Dextrose Injection, Type 1, USP) is not indicated for the treatment of hypochloremic hypokalemic alkalosis. Avoid use in patients with hypochloremic hypokalemic alkalosis.

Hypocalcemia

5% Dextrose and Electrolyte No. 48 Injection (Multiple Electrolytes and Dextrose Injection, Type 1, USP) contains no calcium, and an increase in plasma pH due to its alkalinizing effect may lower the concentration of ionized (not-protein bound) calcium. Avoid 5% Dextrose and Electrolyte No. 48 Injection (Multiple Electrolytes and Dextrose Injection, Type 1, USP) in patients with hypocalcemia.

Hyperkalemia

Potassium-containing solutions, including 5% Dextrose and Electrolyte No. 48 Injection (Multiple Electrolytes and Dextrose Injection, Type 1, USP) may increase the risk of hyperkalemia.

Patient’s at increased risk of developing hyperkalemia include those:

- With conditions predisposing to hyperkalemia and/or associated with increased sensitivity to potassium, such as patients with severe renal impairment, acute dehydration, extensive tissue injury or burns, certain cardiac disorders such as congestive heart failure.
- Treated concurrently or recently with agents or products that cause or increase the risk of hyperkalemia (see PRECAUTIONS).

Avoid 5% Dextrose and Electrolyte No. 48 Injection (Multiple Electrolytes and Dextrose Injection, Type 1, USP) in patients with, or at risk for hyperkalemia. If use cannot be avoided, monitor serum potassium concentrations.

Hyperphosphatemia

5% Dextrose and Electrolyte No. 48 Injection (Multiple Electrolytes and Dextrose Injection, Type 1, USP) may increase the risk of hyperphosphatemia. Avoid use in patients with hyperphosphatemia or conditions predisposing to hyperphosphatemia, such as patients with severe renal or adrenal impairment.

PRECAUTIONS

Patients with Renal Impairment

In patients with renal impairment, administration of 5% Dextrose and Electrolyte No. 48 Injection (Multiple Electrolytes and Dextrose Injection, Type 1, USP) may result in sodium and/or potassium or magnesium retention (see WARNINGS). Avoid 5% Dextrose and Electrolyte No. 48 Injection (Multiple Electrolytes and Dextrose Injection, Type 1, USP) in patients with severe renal impairment or conditions that may cause sodium, potassium, magnesium, or phosphate retention, fluid overload, or edema. If use cannot be avoided, monitor patients with severe renal impairment for development of these adverse reactions.

Patients with Hepatic Impairment

In patients with severe hepatic impairment, lactate metabolism may be impaired and 5% Dextrose and Electrolyte No. 48 Injection (Multiple Electrolytes and Dextrose Injection, Type 1, USP) may not produce its alkalinization. Consider when monitoring serum lactate levels.

Monitoring of Serum Lactate Levels

Administration of 5% Dextrose and Electrolyte No. 48 Injection (Multiple Electrolytes and Dextrose Injection, Type 1, USP) may result in an iatrogenic increase in serum lactate levels in patients with severe metabolic acidosis including lactic.

Drug Interactions

Other Products that Affect Fluid and/or Electrolyte Balance

Administration of 5% Dextrose and Electrolyte No. 48 Injection (Multiple Electrolytes and Dextrose Injection, Type 1, USP) to patients treated concomitantly with drugs associated with sodium and fluid retention may increase the risk of hypernatremia and volume overload. Avoid use of 5% Dextrose and Electrolyte No. 48 Injection (Multiple Electrolytes and Dextrose Injection, Type 1, USP) in patients receiving such products, such as corticosteroids or corticotropin. If use cannot be avoided, monitor serum electrolytes, fluid balance and acid-base balance.

Other Drugs that Increase the Risk of Hyponatremia

Administration of 5% Dextrose and Electrolyte No. 48 Injection (Multiple Electrolytes and Dextrose Injection, Type 1, USP) in patients treated concomitantly with medications associated with hyponatremia may increase the risk of developing hyponatremia.

Avoid use of 5% Dextrose and Electrolyte No. 48 Injection (Multiple Electrolytes and Dextrose Injection, Type 1, USP) in patients receiving products, such as diuretics, and certain antiepileptic and psychotropic medications. Drugs that increase the vasopressin effect reduce renal electrolyte free water excretion and may also increase the risk of hyponatremia following treatment with intravenous fluids. If use cannot be avoided, monitor serum sodium concentrations.

Other Products that Increase the Risk of Hyperkalemia

Because of its potassium content, avoid use of 5% Dextrose and Electrolyte No. 48 Injection (Multiple Electrolytes and Dextrose Injection, Type 1, USP) in patients receiving products that can cause hyperkalemia or increase the risk of hyperkalemia, such as potassium sparing diuretics, ACE inhibitors, angiotensin II receptor antagonists, or the immunosuppressants tacrolimus and cyclosporine. If use cannot be avoided, monitor serum potassium concentrations.

Lithium

Renal clearance of lithium may be increased during administration of 5% Dextrose and Electrolyte No. 48 Injection (Multiple Electrolytes and Dextrose Injection, Type 1, USP). Monitor serum lithium concentrations during concomitant use.

Drugs with pH Dependent Renal Elimination

Due to its alkalinizing effect (formation of bicarbonate), 5% Dextrose and Electrolyte No. 48 Injection (Multiple Electrolytes and Dextrose Injection, Type 1, USP) may interfere with the elimination of drugs with pH dependent renal elimination. Renal clearance of acidic drugs may be increased. Renal clearance of alkaline drugs may be decreased.

Pregnancy

Teratogenic Effects

Animal reproduction studies have not been conducted with 5% Dextrose and Electrolyte No. 48 Injection (Multiple Electrolytes and Dextrose Injection, Type 1, USP).

Intrapartum maternal intravenous infusion of glucose-containing solutions may result in fetal insulin production, with an associated risk of fetal hyperglycemia and metabolic acidosis as well as rebound hypoglycemia in the neonate. 5% Dextrose and Electrolyte No. 48 Injection (Multiple Electrolytes and Dextrose Injection, Type 1, USP) should be given to a pregnant woman by health care providers only after careful consider of the potential risk and benefits for each specific patient.

Pediatric Use

Safety and effectiveness of 5% Dextrose and Electrolyte No. 48 Injection (Multiple Electrolytes and Dextrose Injection, Type 1, USP) in pediatric patients have not been established by adequate and well controlled trials.

The use of 5% Dextrose and Electrolyte No. 48 Injection (Multiple Electrolytes and Dextrose Injection, Type 1, USP) in pediatric patients is based on clinical practice (see DOSAGE AND ADMINISTRATION).

Neonates, especially premature infants with low birth weight, are at increased risk of developing hypo- or hyperglycemia and therefore need close monitoring during treatment with intravenous glucose solutions to ensure adequate glycemic control in order to avoid potential long-term adverse effects. Closely monitor plasma electrolyte concentrations in pediatric patients who may have impaired ability to regulate fluids and electrolytes. In very low birth weight infants, excessive or rapid administration of 5% Dextrose and Electrolyte No. 48 Injection (Multiple Electrolytes and Dextrose Injection, Type 1, USP) may result in increased serum osmolality and risk of intracerebral hemorrhage.

Children (including neonates and older children) are at increased risk of developing hyponatremia as well as for developing hyponatremic encephalopathy.

Lactate-containing solutions should be administered with particular caution to neonates and infants less than 12 months of age. Administration of a lactate-containing intravenous solution to neonates and infants should take into account that the liver and kidneys are still maturing during the first year of life, which also affects the biotransformation and renal excretion of lactate.

Geriatric Use

Geriatric patients are at increased risk of developing electrolyte imbalances. 5% Dextrose and Electrolyte No. 48 Injection (Multiple Electrolytes and Dextrose Injection, Type 1, USP) is known to be substantially excreted by the kidney, and the risk of toxic reactions to this drug may be greater in patients with impaired renal function. Therefore, dose selection for an elderly patient should be cautious, usually starting at the low end of the dosing range, reflecting the greater frequency of decreased hepatic, renal, or cardiac function, and of concomitant disease or other drug therapy. Consider monitoring renal function in elderly patients.

Carcinogenesis, Mutagenesis, Impairment of Fertility

Studies with 5% Dextrose and Electrolyte No. 48 Injection (Multiple Electrolytes and Dextrose Injection, Type 1, USP) have not been performed to evaluate carcinogenic potential, mutagenic potential, or effects on fertility.

Nursing Mothers

It is not known whether this drug is excreted in human milk. Because many drugs are excreted in human milk, caution should be exercised when 5% Dextrose and Electrolyte No. 48 Injection (Multiple Electrolytes and Dextrose Injection, Type 1, USP) is administered to a nursing mother.

ADVERSE REACTIONS

Post-marketing Adverse Reactions

The following adverse reactions associated with the use of 5% Dextrose and Electrolyte No. 48 Injection (Multiple Electrolytes and Dextrose Injection, Type 1, USP) were identified in clinical trials or post marketing reports. Because post marketing reactions were reported voluntarily from a population of uncertain size, it is not always possible to estimate their frequency, reliably, or to establish a causal relationship to drug exposure:

Hypersensitivity and Infusion Reactions: palpitations, feeling abnormal, piloerection, edema peripheral, hypotension, dyspnea, wheezing, urticaria, cold sweet, tachycardia, chest pain, chest discomfort, respiratory rate increased, flushing, hyperemia, asthenia, pyrexia, chills.

General Disorders and Administration Site Conditions: infusion site pain, burning sensation, febrile response, infection at the site of injection, venous thrombosis or phlebitis extending from site of injection, extravasation and hypervolemia.

Metabolism and nutrition disorders: hyperkalemia, hyperglycemia, hyponatremia.

Nervous System Disorders: hyponatremic encephalopathy.

If an adverse reaction does occur, discontinue the infusion, evaluate the patient, institute appropriate therapeutic countermeasures, and save the remainder of the fluid for examination if deemed necessary.

Overdose

Excessive administration of 5% Dextrose and Electrolyte No. 48 Injection (Multiple Electrolytes and Dextrose Injection, Type 1, USP) can cause:

- fluid overload with a risk of edema (peripheral and/or pulmonary), particularly when renal sodium excretion is impaired.
- hyperglycemia, hyperosmolarity, and osmotic diuresis, dehydration and electrolyte loss.
- hypernatremia and hyperkalemia, especially in patients with severe renal impairment.
- hypermagnesemia.
- metabolic alkalosis with or without hypokalemia and decreased ionized serum calcium and magnesium concentrations.
- Hyperphosphatemia, hypocalcemia, and hypomagnesemia. See WARNINGS

When assessing an overdose, any additives in the solution must also be considered.

The effects of an overdose may require immediate medical attention and treatment.

Interventions include discontinuation of 5% Dextrose and Electrolyte No. 48 Injection (Multiple Electrolytes and Dextrose Injection, Type 1, USP), dose reduction, and other measures as indicated for the specific clinical constellation (e.g., monitoring of fluid balance, electrolyte concentrations and acid base balance).

DOSAGE AND ADMINISTRATION

Important Administration Instructions

- 5% Dextrose and Electrolyte No. 48 Injection (Multiple Electrolytes and Dextrose Injection, Type 1, USP) is intended for intravenous administration using sterile equipment.
- Do not connect flexible plastic containers in series in order to avoid air embolism due to possible residual air contained in the primary container.
- Set the vent to the closed position on a vented intravenous administration set to prevent air embolism.
- Use a dedicated line without any connections to avoid air embolism.
- Do not pressurize intravenous solutions contained in flexible plastic containers to increase flow rates in order to avoid air embolism due to incomplete evacuation of residual air in the container.
- Prior to infusion, visually inspect the solution for particulate matter and discoloration. The solution should be clear and there should be no precipitates. Do not administer unless solution is clear, and container is undamaged.
- Do not administer 5% Dextrose and Electrolyte No. 48 Injection (Multiple Electrolytes and Dextrose Injection, Type 1, USP) simultaneously with blood through the same administration set because of the possibility of pseudoagglutination or hemolysis.

Dosing Information

The choice of product, dosage, volume, rate, and duration of administration is dependent upon the age, weight and clinical condition of the patient and concomitant therapy, and administration should be determined by a physician experienced in intravenous fluid therapy.

Introduction of Additives

Additives may be incompatible.

Evaluate all additions to the plastic container for compatibility and stability of the resulting preparation. Consult with a pharmacist, if available.

If, in the informed judgment of the physician, it is deemed advisable to introduce additives, use aseptic technique. Mix thoroughly when additives have been introduced. After addition, if there is a discoloration and/or the appearance of precipitates, insoluble complexes or crystals, do not use. Do not store solutions containing additives. Discard any unused portion.

HOW SUPPLIED

5% Dextrose and Electrolyte No. 48 Injection (Multiple Electrolytes and Dextrose Injection, Type 1, USP) in VIAFLEX plastic containers is available as shown below:

Code | Size (mL) | NDC
2B2103 | 500 | NDC 0338-0143-03

Exposure of pharmaceutical products to heat should be minimized. Avoid excessive heat. It is recommended the product be stored at room temperature (25°C); brief exposure up to 40°C does not adversely affect the product.

DIRECTIONS FOR USE OF VIAFLEX PLASTIC CONTAINERS

For Information on Risk of Air Embolism – see DOSAGE AND ADMINISTRATION

To Open

Tear overwrap down side at slit and remove solution container. Visually inspect the container. If the outlet port protector is damaged, detached, or not present, discard container as solution path sterility may be impaired. Some opacity of the plastic due to moisture absorption during the sterilization process may be observed. This is normal and does not affect the solution quality or safety. The opacity will diminish gradually. Check for minute leaks by squeezing inner bag firmly. If leaks are found, discard solution as sterility may be impaired. If supplemental medication is desired, follow directions below.

Preparation for Administration

1. Suspend container from eyelet support.
2. Remove port protector from outlet port at bottom of container.
3. Attach administration set. Refer to complete directions accompanying set.

To Add Medication

Warning: Additives may be incompatible.

To add medication before solution administration

1. Prepare medication site.
2. Using syringe with 19 to 22 gauge needle, puncture resealable medication port and inject.
3. Mix solution and medication thoroughly. For high density medication such as potassium chloride, squeeze ports while ports are upright and mix thoroughly.

To add medication during solution administration

1. Close clamp on the set.
2. Prepare medication site.
3. Using syringe with 19 to 22 gauge needle, puncture resealable medication port and inject.
4. Remove container from IV pole and/or turn to an upright position.
5. Evacuate both ports by squeezing them while container is in the upright position.
6. Mix solution and medication thoroughly.
7. Return container to in use position and continue administration.

Baxter Healthcare Corporation
Deerfield, IL 60015 USA
Printed in USA

07-19-00-1751

Rev. February 2020

Baxter, VIAFLEX and PL 146 are trademarks of Baxter International Inc.

PRINCIPAL DISPLAY PANEL - PACKAGING LABELING

Container Label

Container Label

Container Label

LOT

EXP

2B2103

NDC 0338-0143-03

5% Dextrose

and Electrolyte

No. 48 Injection

(Multiple Electrolytes and Dextrose
Injection Type 1 USP)

500mL

500 mL

Each 100 mL contains 5 g Dextrose Hydrous USP

260 mg Sodium Lactate 141 mg Potassium Chloride USP

31 mg Magnesium Chloride USP 20 mg Monobasic

Potassium Phosphate NF 12 mg Sodium Chloride USP pH

5.0 (4.0 to 6.5) mEq/L Sodium 25 Potassium 20

Magnesium 3 Chloride 24 Lactate 23 Phosphate(as

HPO4=) 3 Osmolarity 348 mOsmol/L (calc) Sterile

Nonpyrogenic Single dose container Not for use in the

treatment of lactic acidosis Additives may be incompatible

Consult with pharmacist if available When introducing

additives use aseptic technique Mix thoroughly Do not

store Dosage Intravenously as directed by a physician See

directions Cautions Squeeze and inspect inner bag which

maintains product sterility Discard if leaks are found

Must not be used in series connections Do not administer

simultaneously with blood Do not use unless solution is

clear Rx Only Store unit in moisture barrier overwrap at

room temperature (25ºC/77ºF) until ready to use

Avoid excessive heat insert

VIAFLEX container PL 146 plastic

BAXTER VIAFELX and PL 146 are trademarks of

Baxter International Inc

For product information 1-800-933-0303

Baxter Logo

Baxter Healthcare Corporation

Deerfield, IL 60015 USA

Made in USA